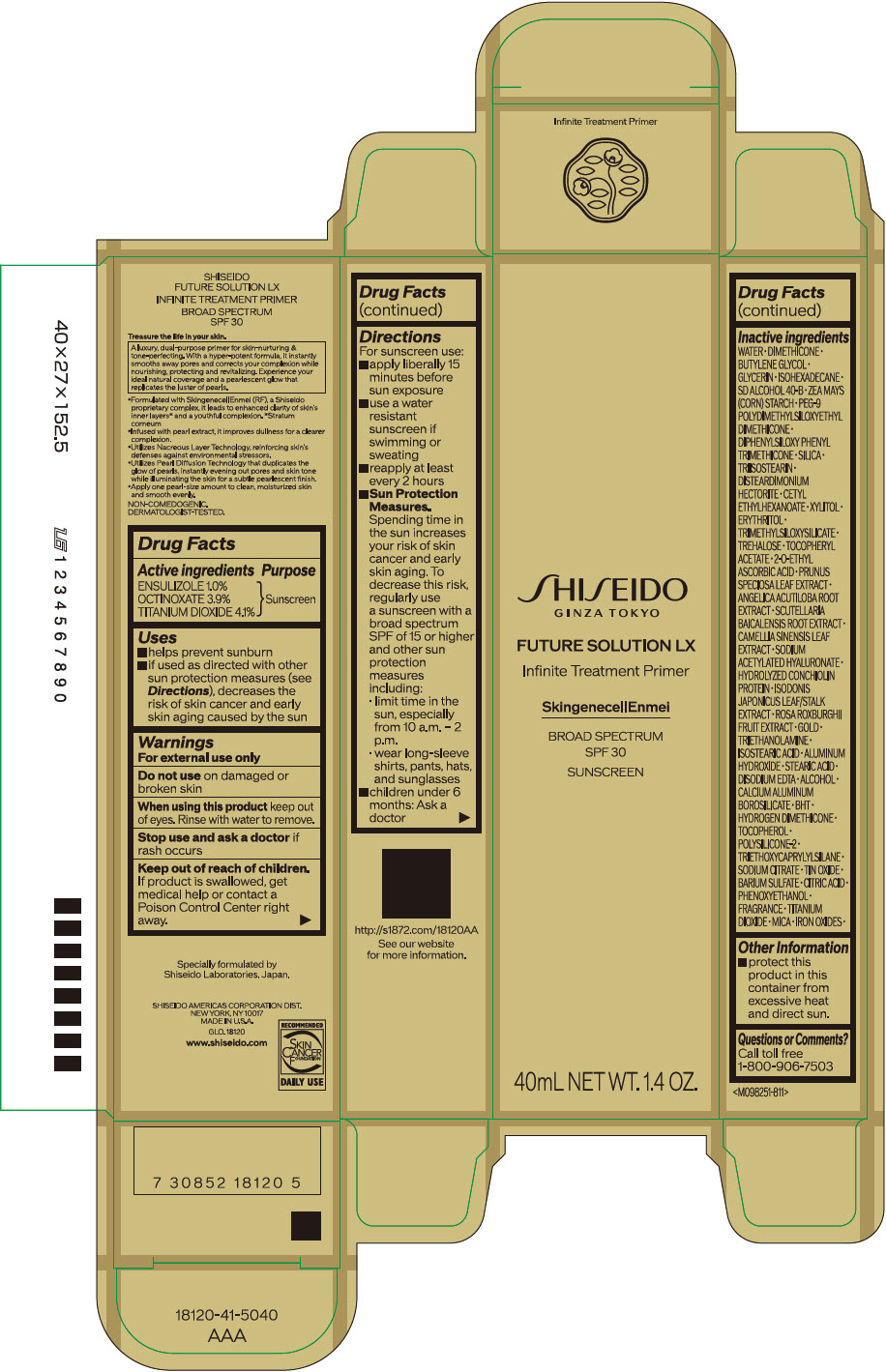 DRUG LABEL: SHISEIDO FUTURE Solution LX INFINITE TREATMENT PRIMER
NDC: 58411-657 | Form: EMULSION
Manufacturer: SHISEIDO AMERICAS CORPORATION
Category: otc | Type: HUMAN OTC DRUG LABEL
Date: 20260106

ACTIVE INGREDIENTS: TITANIUM DIOXIDE 1.77 g/40 mL; OCTINOXATE 1.71 g/40 mL; ENSULIZOLE 0.428 g/40 mL
INACTIVE INGREDIENTS: GREEN TEA LEAF; SODIUM ACETYLATED HYALURONATE; BARIUM SULFATE; CITRIC ACID MONOHYDRATE; ROSA ROXBURGHII FRUIT; GOLD; STEARIC ACID; EDETATE DISODIUM; FERRIC OXIDE RED; FERRIC OXIDE YELLOW; FERROSOFERRIC OXIDE; ALCOHOL; .ALPHA.-TOCOPHEROL ACETATE, DL-; CALCIUM ALUMINUM BOROSILICATE; BUTYLATED HYDROXYTOLUENE; 2-O-ETHYL ASCORBIC ACID; HYDROGEN DIMETHICONE (13 CST); .ALPHA.-TOCOPHEROL; TRIETHOXYCAPRYLYLSILANE; SODIUM CITRATE, UNSPECIFIED FORM; STANNIC OXIDE; PRUNUS SPECIOSA LEAF; ANGELICA ACUTILOBA ROOT; WATER; DIMETHICONE; BUTYLENE GLYCOL; GLYCERIN; ISOHEXADECANE; PEG-9 POLYDIMETHYLSILOXYETHYL DIMETHICONE; DIPHENYLSILOXY PHENYL TRIMETHICONE; STARCH, CORN; SILICON DIOXIDE; TRIISOSTEARIN; DISTEARDIMONIUM HECTORITE; XYLITOL; CETYL ETHYLHEXANOATE; TROLAMINE; TRIMETHYLSILOXYSILICATE (M/Q 0.6-0.8); ERYTHRITOL; MICA; ISOSTEARIC ACID; PHENOXYETHANOL; TREHALOSE; ALUMINUM HYDROXIDE; SCUTELLARIA BAICALENSIS ROOT

SHISEIDO FUTURE SOLUTION LX INFINITE TREATMENT PRIMER

Drug Facts

ACTIVE INGREDIENT

Active ingredients | Purpose
ENSULIZOLE 1.0% | Sunscreen
OCTINOXATE 3.9% | Sunscreen
TITANIUM DIOXIDE 4.1% | Sunscreen

Uses

- helps prevent sunburn
- if used as directed with other sun protection measures (see Directions), decreases the risk of skin cancer and early skin aging caused by the sun

Warnings

For external use only

Do not use on damaged or broken skin

WHEN USING

When using this productkeep out of eyes. Rinse with water to remove.

Stop use and ask a doctorif rash occurs.

Keep out of reach of children.If product is swallowed, get medical help or contact a Poison Control Center right away.

Directions

For sunscreen use:

- apply liberally 15 minutes before sun exposure
- use a water resistant sunscreen if swimming or sweating
- reapply at least every two hours
- Sun Protection Measures.
  Spending time in the sun increases your risk of skin cancer and early skin aging. To decrease this risk, regularly use a sunscreen with a broad spectrum SPF of 15 or higher and other sun protection measures including:
  - limit time in the sun, especially from 10 a.m. – 2 p.m.
  - wear long-sleeve shirts, pants, hats, and sunglasses
- children under 6 months: Ask a doctor

Inactive Ingredients

WATER∙DIMETHICONE∙BUTYLENE GLYCOL∙GLYCERIN∙ISOHEXADECANE∙SD ALCOHOL 40-B∙ZEA MAYS (CORN) STARCH∙PEG-9 POLYDIMETHYLSILOXYETHYL DIMETHICONE∙DIPHENYLSILOXY PHENYL TRIMETHICONE∙SILICA∙TRIISOSTEARIN∙DISTEARDIMONIUM HECTORITE∙CETYLETHYLHEXANOATE∙XYLITOL∙ERYTHRITOL∙TRIMETHYLSILOXYSILICATE∙TREHALOSE∙TOCOPHERYL ACETATE∙2-O-ETHYL ASCORBIC ACID∙PRUNUS SPECIOSA LEAF EXTRACT∙ANGELICA ACUTILOBA ROOT EXTRACT∙SCUTELLARIA BAICALENSIS ROOT EXTRACT∙CAMELLIA SINENSIS LEAF EXTRACT∙SODIUM ACETYLATED HYALURONATE∙ISODONIS JAPONICUS LEAF/STALK EXTRACT∙HYDROLYZED CONCHIOLIN PROTEIN∙ROSA ROXBURGHII FRUIT EXTRACT∙GOLD∙TRIETHANOLAMINE∙ISOSTEARIC ACID∙ALUMINUM HYDROXIDE∙STEARIC ACID∙DISODIUM EDTA∙ALCOHOL∙CALCIUM ALUMINUM BOROSILICATE∙BHT∙HYDROGEN DIMETHICONE∙TOCOPHEROL∙POLYSILICONE-2∙TRIETHOXYCAPRYLYLSILANE∙SODIUM CITRATE∙TIN OXIDE∙BARIUM SULFATE∙CITRIC ACID∙PHENOXYETHANOL∙FRAGRANCE∙TITANIUM DIOXIDE∙MICA∙IRON OXIDES

Other information

Protect this product in this container from excessive heat and direct sun.

Questions or comments?

Call toll free 1-800-906-7503

PRINCIPAL DISPLAY PANEL - 40 mL Tube Carton

SHISEIDO
GINZA TOKYO

FUTURE SOLUTION LX
Infinite Treatment Primer

SkingenecellEnmei

BROAD SPECTRUM
SPF 30
SUNSCREEN

40mL NET WT. 1.4 OZ.